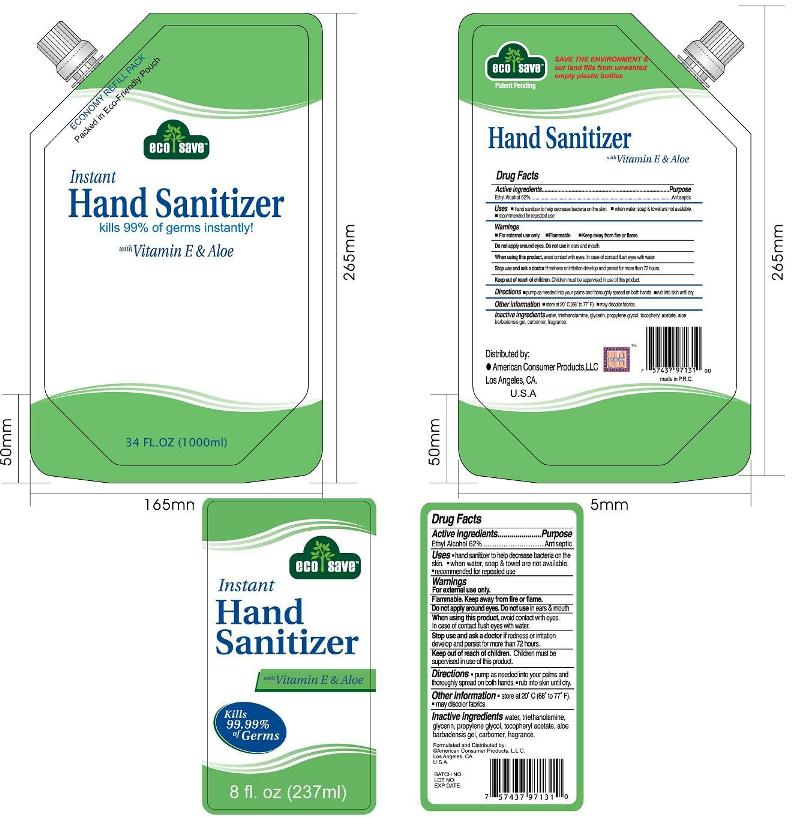 DRUG LABEL: INSTANT HAND SANITIZER
NDC: 18018-501 | Form: KIT | Route: TOPICAL
Manufacturer: NINGBO CLEANER DAILY USED PRODUCTS CO. LTD.
Category: otc | Type: HUMAN OTC DRUG LABEL
Date: 20091101

ACTIVE INGREDIENTS: ALCOHOL 62 mL/100 mL; ALCOHOL 62 mL/100 mL
INACTIVE INGREDIENTS: WATER; TROLAMINE; GLYCERIN; PROPYLENE GLYCOL; ALPHA-TOCOPHEROL; WATER; TROLAMINE; GLYCERIN; PROPYLENE GLYCOL; ALPHA-TOCOPHEROL

ECO-SAVE INSTANT HAND SANITIZER

Drug Facts

Active Ingredients

Ethyl Alcohol 62%

Purpose

Antiseptic

Warnings

For external use only

- flammable, keep away from fire and flame
- will produce serious gastric disturbances if taken internally

Ask a doctor before use if you have deep puncture wounds or serious burns

When using this product

- do not get into eyes or mucous membranes
- use only in a well-ventilated area

Stop use and ask a doctor if condition persists or gets worse.

Keep out of reach of children. In case of an accidental ingestion, contact a Poison Control Center immediately.

Uses

hand sanitizer to help decrease bacteria on the skin. when water, soap and towel are not available. recommended for repeated use

Warnings

- For external use only
- Flammable
- Keep away from fire or flame

DO NOT USE

Do not apply around eyes. Do not use in ears and mouth.

When using this product, avoid contact with eyes. In case of contact flush eyes with water.

Stop use and ask a doctor if redness or irritation develop and persist for more than 72 hours.

Keep out of reach of children. Children must be supervised in use of this product.

Directions

pump as needed into your palms and thoroughly spread on both hands. rub skin until dry.

Other information

store at 20 degree celsius (68 degrees to 77 degrees fahrenheit). may discolor fabrics.

Inactive ingredients

water, triethanolamine, glycerin, propylene glycol, tocopheryl acetate, aloe barbadensis gel, carbomer, fragrance